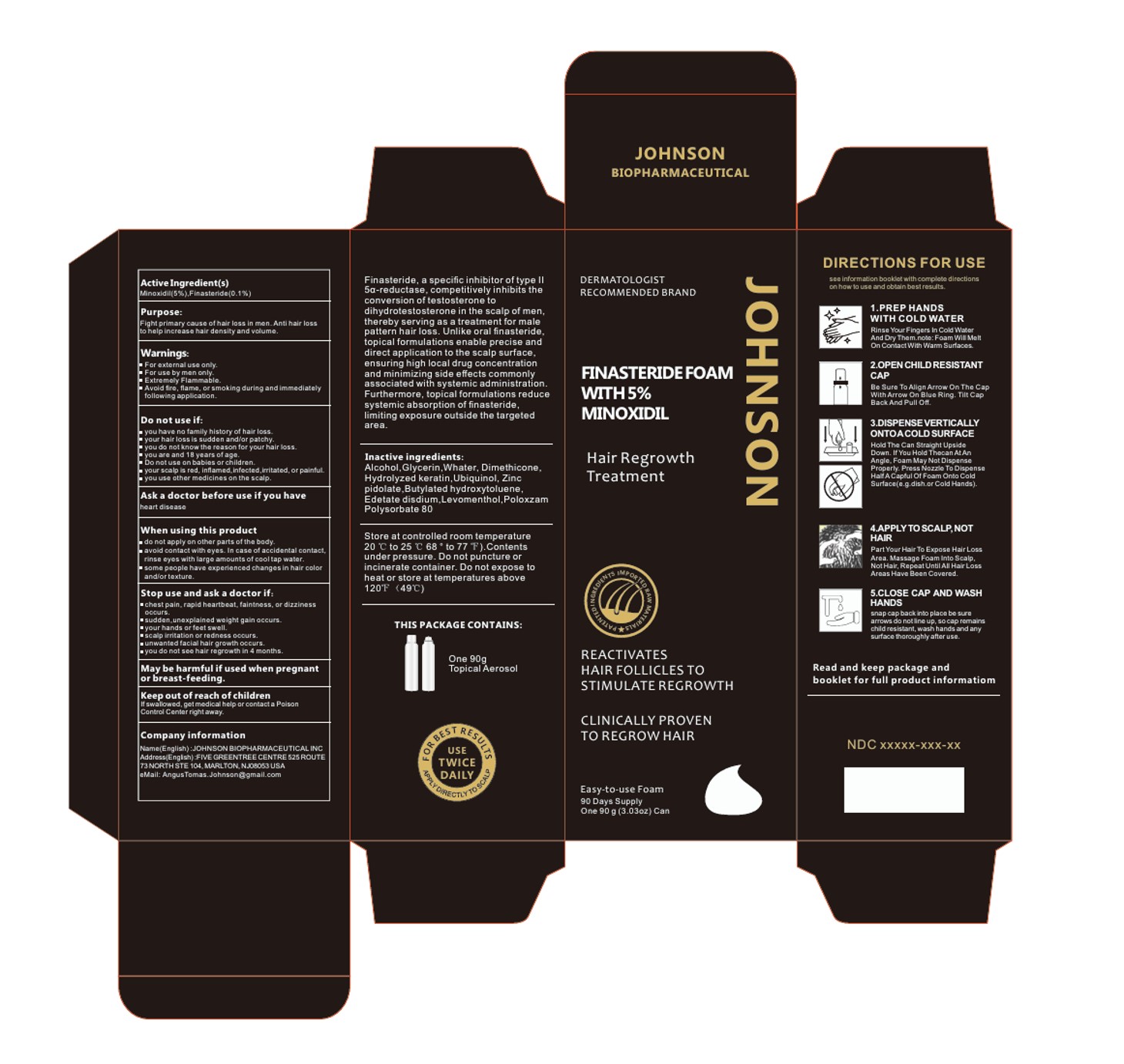 DRUG LABEL: JOHNSON FOAM
NDC: 84539-001 | Form: AEROSOL, FOAM
Manufacturer: JOHNSON BIOPHARMACEUTICAL INC.
Category: otc | Type: HUMAN OTC DRUG LABEL
Date: 20250611

ACTIVE INGREDIENTS: FINASTERIDE 0.1 g/100 g; MINOXIDIL 5 g/100 g
INACTIVE INGREDIENTS: EDETATE DISODIUM; ALCOHOL; GLYCERIN; WATER; UBIQUINOL; ZINC PIDOLATE; BUTYLATED HYDROXYTOLUENE; CETYL PEG/PPG-10/1 DIMETHICONE (HLB 5); LEVOMENTHOL; POLOXAMER 407; POLYSORBATE 80

JOHNSON FOAM

ACTIVE INGREDIENT

MINOXIDIL 5%
FINASTERIDE 0.1%

PURPOSE

Fight primary cause of hair loss in men. Anti hair loss
to help increase hair densityand volume.

KEEP OUT OF REACH OF CHILDREN

Keep out of reach of childrenIfswallowed,get medical help or contact a PoisonControlCenter rightaway

INDICATIONS AND USAGE

Fight primary cause of hair loss in men.Anti hair lossto help increase hair density and volume
do not apply on other parts of the body.
avoid contactwith eyes.In case of accidental contactrinse eyes with large amounts of cool tap water.
some people have experienced changes in hair colorand/or texture

WARNINGS

For external use only
For use by men only.
Extremely Flammable
Avoid fire, flame, or smoking during and immediatelyfollowing application.

DOSAGE AND ADMINISTRATION

1.PREP HANDSWITH COLD WATERRinse Your Fingers In Cold WaterAnd DryThem.note:Foam Will MeltOn Contact With Warm Surfaces.

2.OPEN CHILDRESISTANT CAP
Be Sure To Align Arrow On The capWith Arrow On Blue Ring. Tilt CapBack And Pull Off.

3.DISPENSEVERTICALLYONTOACOLD SURFACE
Hold The Can Straight UpsideDown.lf You Hold Thecan At AnAngle, Foam May Not DispenseProperly.Press Nozzle To DispenseHalfACapful Of Foam Onto ColdSurface(e.g.dish.or Cold Hands).

4.APPLYTOSCALP.NOT HAIR
Part Your Hair To Expose Hair LossArea.Massage Foam Into ScalpNot Hair, Repeat UntilAll HairLossAreas Have Been Covered.

5.CLOSE CAP AND WASHHANDSsnap cap back into place be surearrows do not line up, so cap remainschild resistant, wash hands and anysurface thoroughly afteruse

STORAGE AND HANDLING

Store at controlledroom temperature20 ℃ to 25 ℃68°to 77 F).Contentsunder pressure.Do not puncture orincinerate container. Do not expose toheat or store at temperatures above120F(49℃)

INACTIVE INGREDIENT

ALCOHOL
GLYCERIN
WHATER
CETYL PEG/PPG-10/1 DIMETHICONE (HLB 5)
UBIQUINOL
ZINC PIDOLATE
BUTYLATED HYDROXYTOLUENE
EDETATE DISODIUM
LEVOMENTHOL
Poloxzam
POLYSORBATE 80